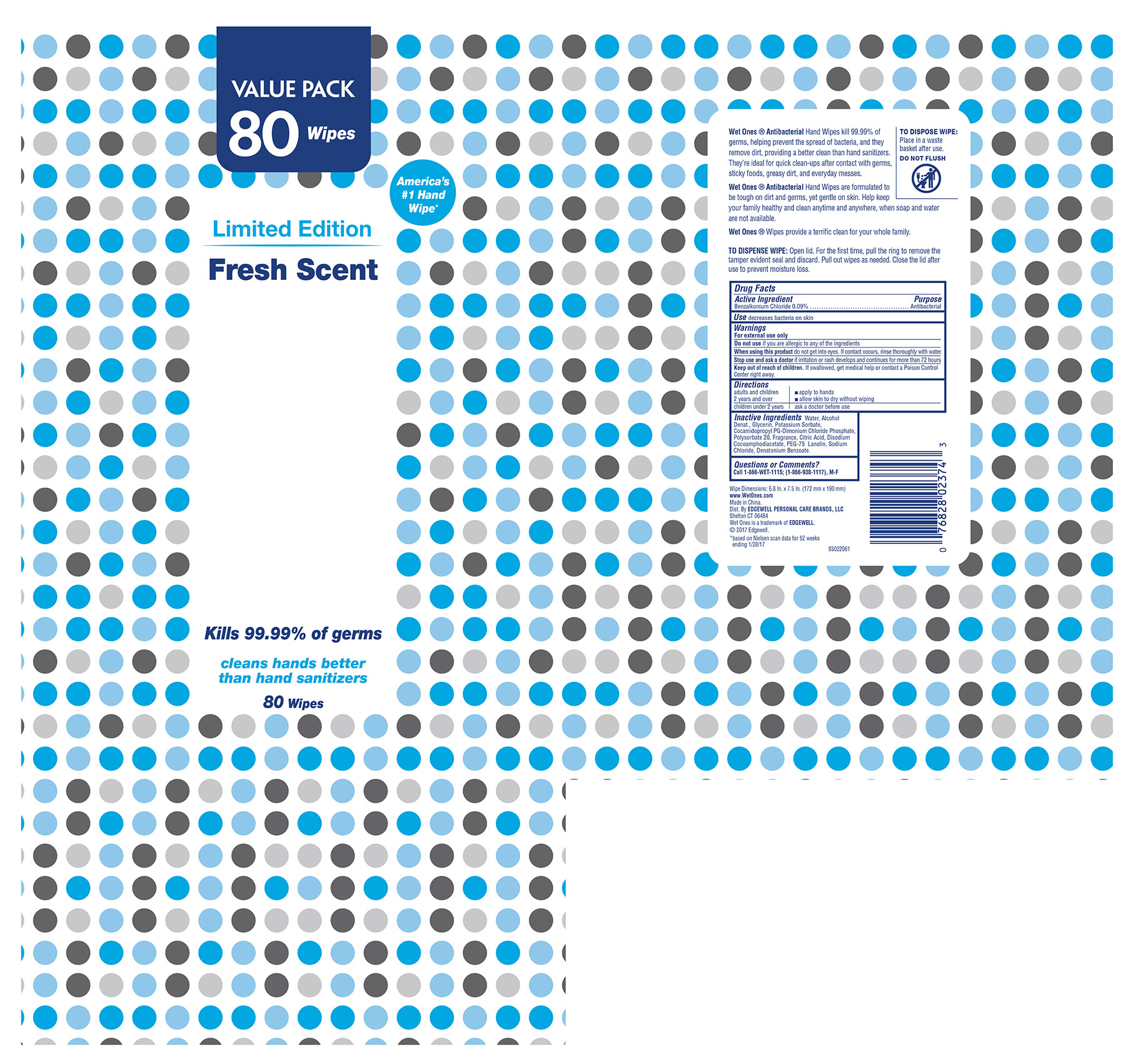 DRUG LABEL: Wet Ones
NDC: 30493-001 | Form: CLOTH
Manufacturer: FOSHAN CITY SHUNDE AREA SOSHIO WET TISSUE CO., LTD.
Category: otc | Type: HUMAN OTC DRUG LABEL
Date: 20170814

ACTIVE INGREDIENTS: BENZALKONIUM CHLORIDE 0.09 g/1 1
INACTIVE INGREDIENTS: WATER; ALCOHOL; GLYCERIN; POTASSIUM SORBATE; ANHYDROUS CITRIC ACID; COCAMIDOPROPYL PG-DIMONIUM CHLORIDE PHOSPHATE; POLYSORBATE 20; CITRIC ACID MONOHYDRATE; DENATONIUM BENZOATE; DISODIUM COCOAMPHODIACETATE; PEG-75 LANOLIN; SODIUM CHLORIDE

Drug Facts

Active Ingredient

Benzalkonium Chloride 0.09%

Purpose

Antibacterial

Use

decreases bacteria on the skin

Warnings

For external use only

Do not use

if you are allergic to any of the ingredients

When using this product

do not get into eyes. If eye contact occurs, rinse thoroughly with water.

Stop use and ask a doctor if

if irritation or rash develops and continues for more than 72 hours.

Keep out of reach of children

if swallowed, get medical help or contact a Poison Control Center right away.

Directions

adults and children ■ apply to hands

2 years and over ■ allow skin to dry without wiping

children under 2 years ask a doctor

Inactive Ingredients

Water, Alcohol Denat., Glycerin, Potassium Sorbate, Cocamidopropyl PG-Dimonium Chloride Phosphate, Polysorbate 20, Fragrance, Citric Acid, Disodium Cocoamphodiacate, PEG-75 Lanolin, Sodium Chloride, Denatonium Benzoate

Questions or Comments?

Call 1-866-WET-111S; (1-866-938-1117), M-F